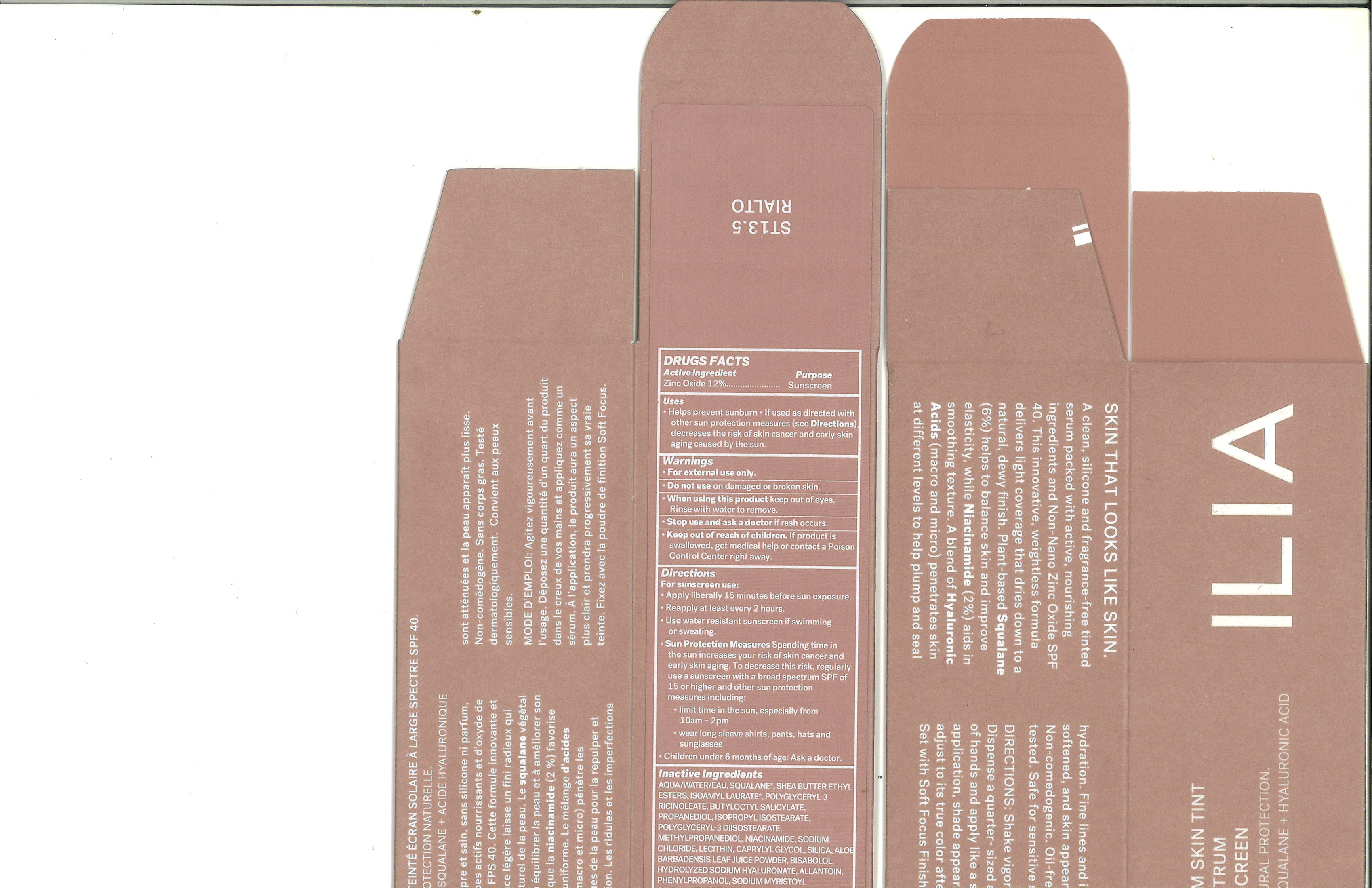 DRUG LABEL: ILIA SUPER SERUM SKIN TINT (ST13.5 RIALTO)
NDC: 81110-056 | Form: LOTION
Manufacturer: Ilia, Inc.
Category: otc | Type: HUMAN OTC DRUG LABEL
Date: 20251030

ACTIVE INGREDIENTS: ZINC OXIDE 132 mg/1 mL
INACTIVE INGREDIENTS: ISOAMYL LAURATE; SHEA BUTTER; POLYGLYCERYL-3 DIISOSTEARATE; ISOPROPYL ISOSTEARATE; .ALPHA.-BISABOLOL, (+)-; CAPRYLYL GLYCOL; LECITHIN, SOYBEAN; ALOE VERA LEAF; ALLANTOIN; SILICON DIOXIDE; SQUALANE; BUTYLOCTYL SALICYLATE; HYALURONATE SODIUM; TITANIUM DIOXIDE; SODIUM MYRISTOYL GLUTAMATE; ALUMINUM HYDROXIDE; WATER; NIACINAMIDE; PROPANEDIOL; SODIUM CHLORIDE; PHENYLPROPANOL; METHYLPROPANEDIOL

ILIA SUPER SERUM SKIN TINT (ST13.5 RIALTO)